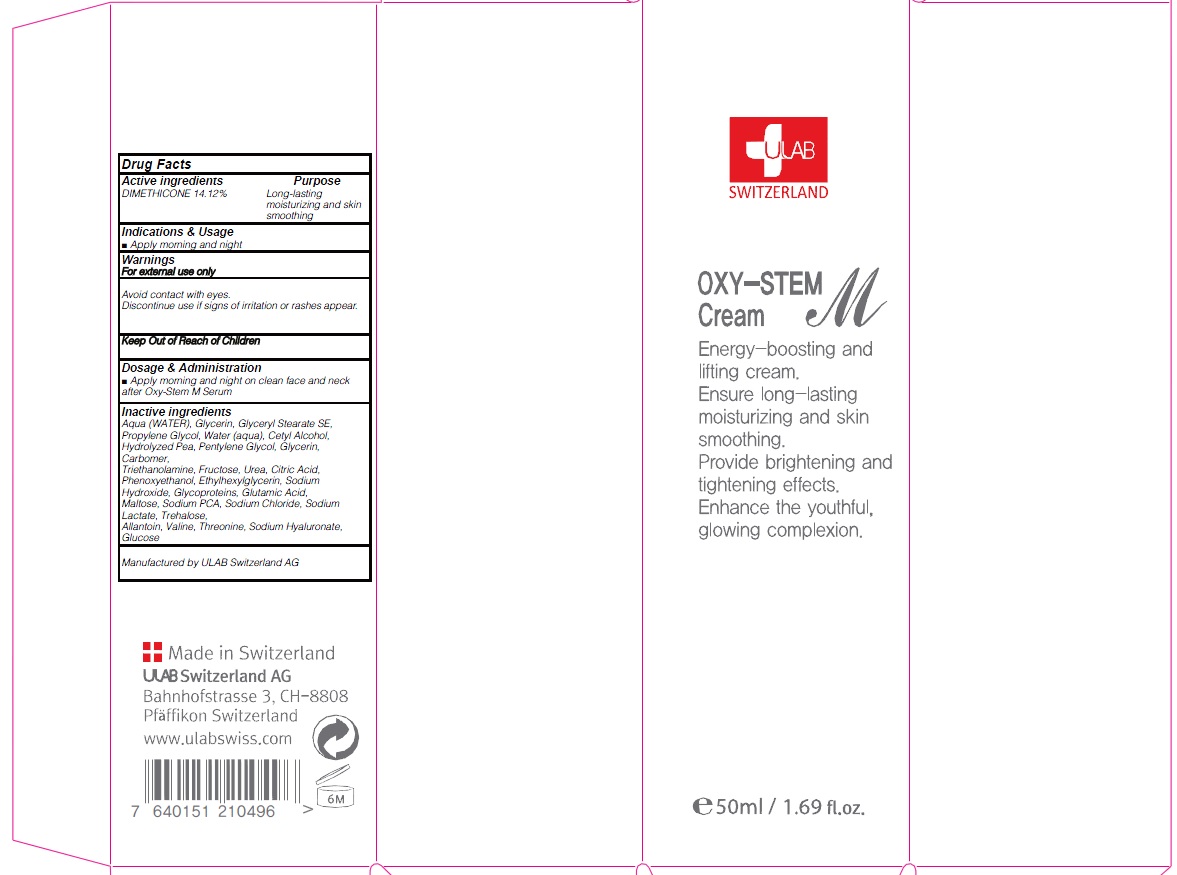 DRUG LABEL: OXY STEM M
NDC: 71276-080 | Form: CREAM
Manufacturer: ULAB
Category: otc | Type: HUMAN OTC DRUG LABEL
Date: 20170322

ACTIVE INGREDIENTS: DIMETHICONE 7.06 g/50 mL
INACTIVE INGREDIENTS: WATER; Glycerin

ACTIVE INGREDIENT

Active ingredients: DIMETHICONE 14.12%

INACTIVE INGREDIENT

Inactive ingredients: Aqua (WATER), Glycerin, Glyceryl Stearate SE, Propylene Glycol, Water (aqua), Cetyl Alcohol, Hydrolyzed Pea, Pentylene Glycol, Glycerin, Carbomer, Triethanolamine, Fructose, Urea, Citric Acid, Phenoxyethanol, Ethylhexylglycerin, Sodium Hydroxide, Glycoproteins, Glutamic Acid, Maltose, Sodium PCA, Sodium Chloride, Sodium Lactate, Trehalose, Allantoin, Valine, Threonine, Sodium Hyaluronate, Glucose

PURPOSE

Purpose: Long-lasting moisturizing and skin smoothing

WARNINGS

Warnings: For external use only Avoid contact with eyes. Discontinue use if signs of irritation or rashes appear.

KEEP OUT OF REACH OF CHILDREN

INDICATIONS & USAGE

Indications & Usage: Apply morning and night

DOSAGE & ADMINISTRATION

Dosage & Administration: Apply morning and night on clean face and neck after Oxy-Stem M Serum